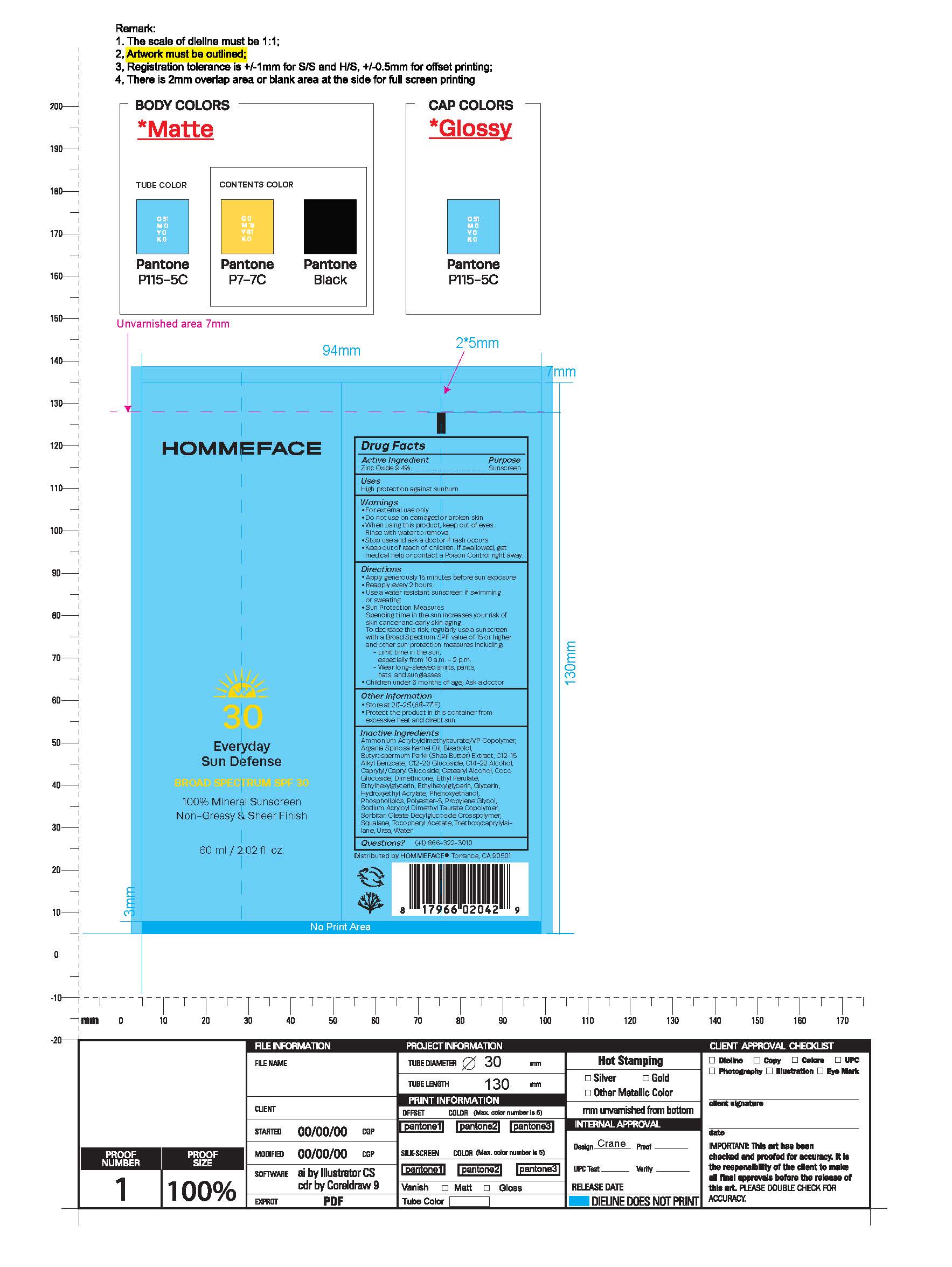 DRUG LABEL: Everyday Sun Defense
NDC: 83580-010 | Form: CREAM
Manufacturer: Hommerejuvenate, Inc.
Category: otc | Type: HUMAN OTC DRUG LABEL
Date: 20251121

ACTIVE INGREDIENTS: ZINC OXIDE 9.4 g/9.4 g
INACTIVE INGREDIENTS: ARGAN OIL; ETHYL FERULATE; PHENOXYETHANOL; AMMONIUM ACRYLOYLDIMETHYLTAURATE/VP COPOLYMER; SQUALANE; CETOSTEARYL ALCOHOL; CAPRYLYL/CAPRYL OLIGOGLUCOSIDE; TRIETHOXYCAPRYLYLSILANE; WATER; .ALPHA.-TOCOPHEROL ACETATE, D-; SODIUM CHLORIDE; ALPHA-TOCOPHEROL ACETATE; GLYCERIN; PROPYLENE GLYCOL; HYDROXYETHYL ACRYLATE/SODIUM ACRYLOYLDIMETHYL TAURATE COPOLYMER (45000 MPA.S AT 1%); DIMETHICONE; ALKYL (C12-15) BENZOATE; COCO GLUCOSIDE; C14-22 ALCOHOLS; C12-20 ALKYL GLUCOSIDE; ETHYLHEXYLGLYCERIN; OMEGA-3 FATTY ACIDS; GLUCONOLACTONE; BENZYL ALCOHOL; SORBIC ACID; SODIUM BENZOATE; SHEA BUTTER; UREA; CHLORPHENESIN; POLYESTER-5 (TG-38); LEVOMENOL

Everyday Sun Defense

Active Ingredient

Zinc Oxide 9.4%

Inactive Ingredient

Ammonium Acryloyldimethyltaurate/VP Copolymer, Argania Spinosa Kernel Oil, Bisabolol, Butyrospermum Parkii (Shea Butter) Extract, C12-15 Alkyl Benzoate, C12-20 Glucoside, C14-22 Alcohol, Caprylyl/Capryl Glucoside, Cetearyl Alcohol, Coco Glucoside, Dimethicone, Ethyl Ferulate, Ethylhexylglycerin, Ethylhexylglycerin, Glycerin, Hydroxyethyl Acrylate, Phenoxyethanol, Phospholipids, Polyester-5, Propylene Glycol, Sodium Acryloyl Dimethyl Taurate Copolymer, Sorbitan Oleate Decylglucoside Crosspolymer, Squalane, Tocopheryl Acetate, Triethoxycaprylylsi-lane, Urea, Water

OTC-Ask Doctor

Ask a doctor if rash occurs

OTC-Do Not Use

Do not use on damaged or broken skin

OTC-Keep Out of Reach of Children

Keep out of reach of children. If swallowed, get medical help or contact Poison Control right away

OTC-Purpose

Sunscreen

OTC-Questions

+1) 866-322-3010

OTC-Stop Use

Stop use if rash occurs

OTC-When using

When using this product keep out of eyes
Rinse with water to remove

Indications & Usage Section

High protection against sunburn

WARNINGS

- For external use only
- Do not use on damaged or broken skin
- When using this product, keep out of eyes.
- Rinse with water to remove.
- Stop use and ask a doctor if rash occurs
- Keep out of reach of children. If swallowed, get medical help or contact a Poison Control right away

DOSAGE AND ADMINISTRATION

- Apply generously 15 minutes before sun exposure

- Reapply every 2 hours
- Use a water-resistant sunscreen if swimming or sweating